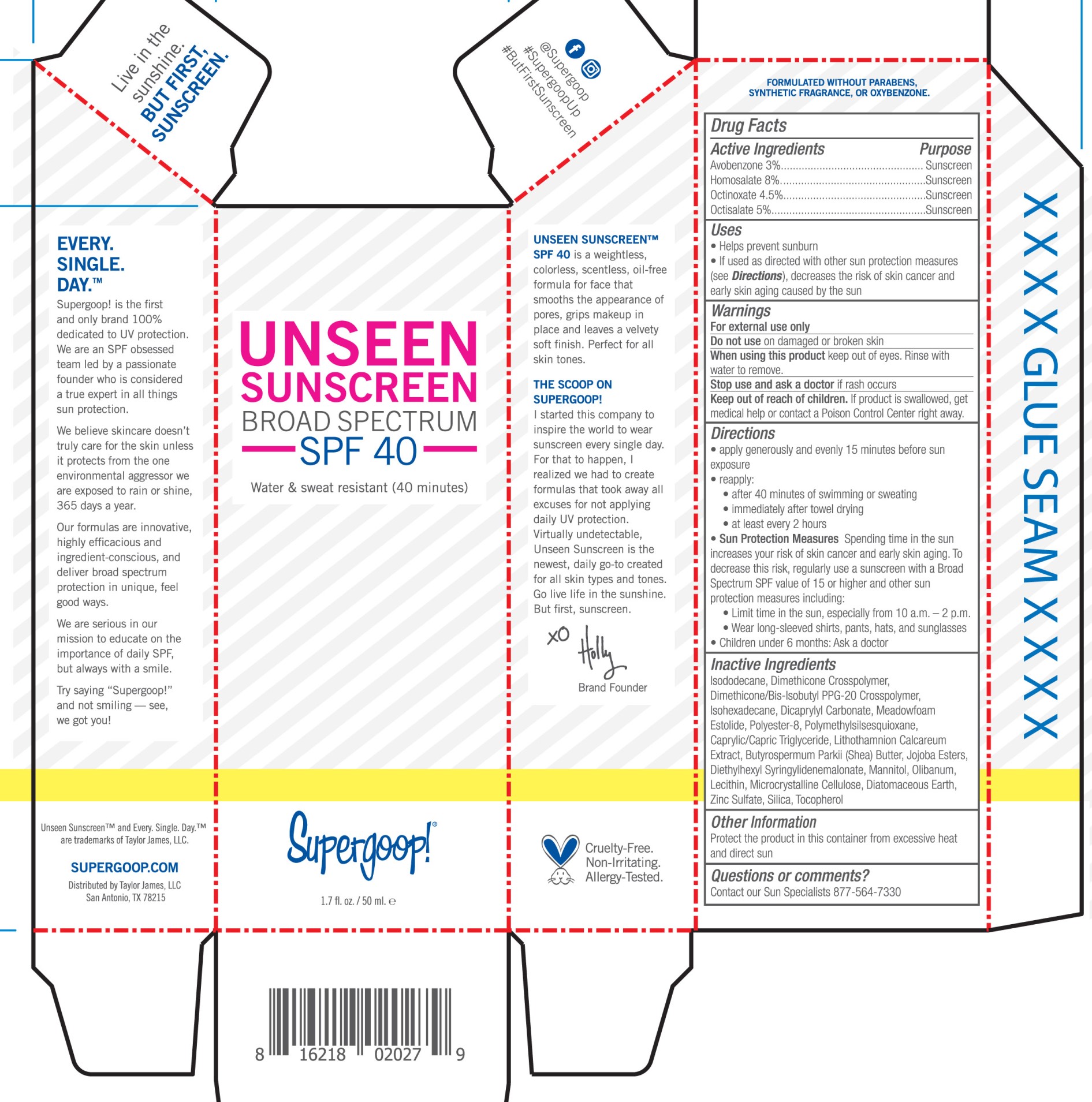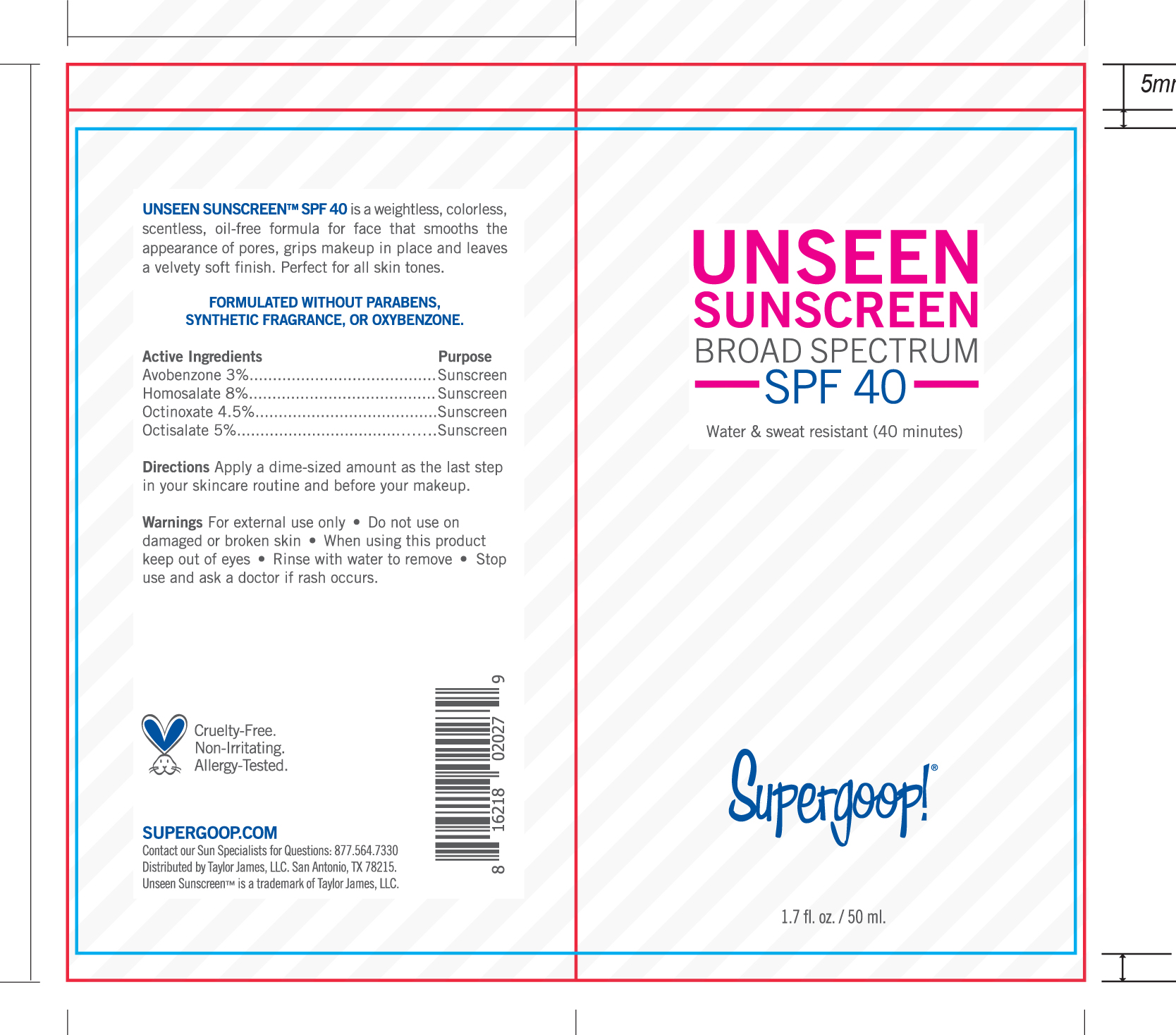 DRUG LABEL: Unseen Sunscreen Broad Spectrum SPF 40
NDC: 75936-142 | Form: CREAM
Manufacturer: TAYLOR JAMES, LTD.
Category: otc | Type: HUMAN OTC DRUG LABEL
Date: 20210106

ACTIVE INGREDIENTS: AVOBENZONE 3 g/100 mL; HOMOSALATE 8 g/100 mL; OCTINOXATE 4.5 g/100 mL; OCTISALATE 5 g/100 mL
INACTIVE INGREDIENTS: ISODODECANE; DIMETHICONE CROSSPOLYMER (450000 MPA.S AT 12% IN CYCLOPENTASILOXANE); DIMETHICONE/BIS-ISOBUTYL PPG-20 CROSSPOLYMER; ISOHEXADECANE; DICAPRYLYL CARBONATE; POLYESTER-8 (1400 MW, CYANODIPHENYLPROPENOYL CAPPED); POLYMETHYLSILSESQUIOXANE (11 MICRONS); MEDIUM-CHAIN TRIGLYCERIDES; PHYMATOLITHON CALCAREUM; SHEA BUTTER; DIETHYLHEXYL SYRINGYLIDENEMALONATE; MANNITOL; FRANKINCENSE; LECITHIN, SUNFLOWER; MICROCRYSTALLINE CELLULOSE; DIATOMACEOUS EARTH; ZINC SULFATE; SILICON DIOXIDE; TOCOPHEROL

Unseen Sunscreen Broad Spectrum SPF 40

Active Ingredients Purpose

Avobenzone 3% Sunscreen

Homosalate 8% Sunscreen

Octinoxate 4.5% Sunscreen

Octisalate 5% Sunscreen

Uses

- Helps prevent sunburn
- If used as directed with other sun protection measures (see Directions), decreases the risk of skin cancer and early skin aging caused by the sun

Keep out of reach of children. If product is swallowed, get medical help or contact a Poison Control Center right away.

Stop use and ask a doctor if rash occurs

Warnings

For external use only

Do not use on damaged or broken skin

Directions

- apply generously and evenly 15 minutes before sun exposure
- reapply:

after 40 minutes of swimming or sweating

immediately after towel drying

at least every 2 hours

- Sun Protection Measures Spending time in the sun increases your risk of skin cancer and early skin aging. To decrease this risk, regularly use a sunscreen with a Broad Spectrum SPF value of 15 or higher and other sun protection measures including:
- Limit time in the sun, especially from 10 a.m.-2 p.m.
- Wear long-sleeved shirts, pants, hats, and sunglasses
- Children under 6 months: ask a doctor

Inactive Ingredients

Isododecane, Dimethicone Crosspolymer, Dimethicone/Bis-Isobutyl PPG-20 Crosspolymer, Isohexadecane, Dicrapylyl Carbonate, Meadowfoam Estolide, Polyester-8,Polymethylsilsesquioxane, Caprylic/Capric Triglyceride, Lithothamnion Calcareum Extract,Butyrospermum Parkii (Shea) Butter, Jojoba Esters, Diethylhexyl Syringylidenemalonate, Mannitol, Olibanum, Lecithin, Microcrystalline Cellulose, Diatomaceous Earth, Zinc Sulfate, Silica, Tocopherol

PACKAGE LABEL

Unseen Sunscreen

Broad Spectrum SPF 40

Water and sweat resistant (40 minutes)

1.7 fl oz/ 50 ml